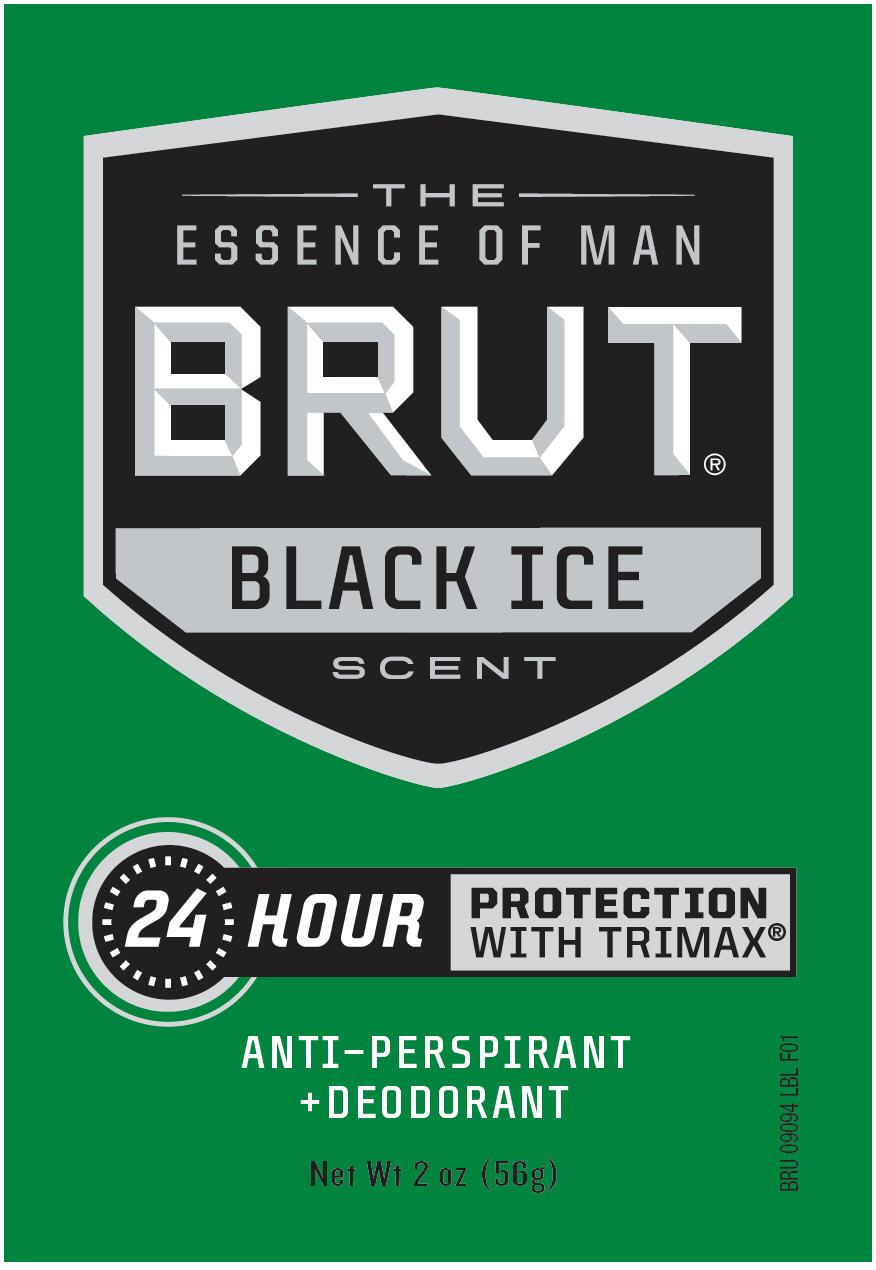 DRUG LABEL: Brut Black Ice
NDC: 41595-7008 | Form: STICK
Manufacturer: Idelle Labs, Ltd
Category: otc | Type: HUMAN OTC DRUG LABEL
Date: 20131126

ACTIVE INGREDIENTS: ALUMINUM ZIRCONIUM TETRACHLOROHYDREX GLY 19 g/100 g
INACTIVE INGREDIENTS: BUTYLATED HYDROXYTOLUENE; CITRIC ACID MONOHYDRATE; CYCLOMETHICONE 5; GLYCERYL MONOOLEATE; HYDROGENATED CASTOR OIL; HYDROQUINONE; PEG-8 DISTEARATE; PPG-14 Butyl Ether; PROPYLENE GLYCOL; STEARYL ALCOHOL; TALC; T-BUTYLHYDROQUINONE; CORN OIL

Brut Black Ice Anti-perspirant and Deodorant

The Essence of Man
BRUT BLACK ICE Scent
24-Hour Protection With Trimax
Antiperspirant & Deodorant
Net Wt 2 oz (56g)
Long Lasting Wetness and Odor Protection

Active Ingredient

Aluminum Zirconium Tetrachlorohydrex Gly 19% (anhydrous)

Purpose

Antiperspirant

Uses

Reduces underarm wetness

Warnings:

For external use only

Stop use

and ask a doctor if rash or irritation develops

Do not use

on broken skin

Keep out of reach of children.

In case of ingestion, get medical help or contact a Poison Control Center right away.

Ask a doctor

before use if you have kidney disease.

Directions

apply to underarms only

Inactive Ingredients

BHT, citric acid, cyclopentasiloxane, fragrance, glyceryl oleate, hydrogenated castor oil, hydroquinone, PEG-8 distearate, PPG-14 butyl ether, propylene glycol, stearyl alcohol, talc, t-butyl hydroquinone, vegetable oil

Questions?

Call 1-800-487-7273 www.brutworld.com

©Idelle Labs, Ltd. All Rights Reserved.BRUT, Essence Of Man and TRIMAX are registered trademarks of Helen of Troy Limited.
Made in Canada
Distributed by Idelle Labs Ltd, El Paso, TX 79912 USA

label